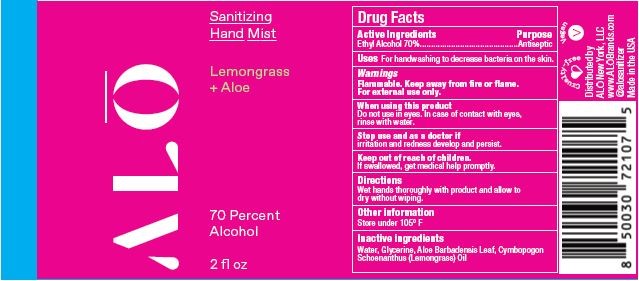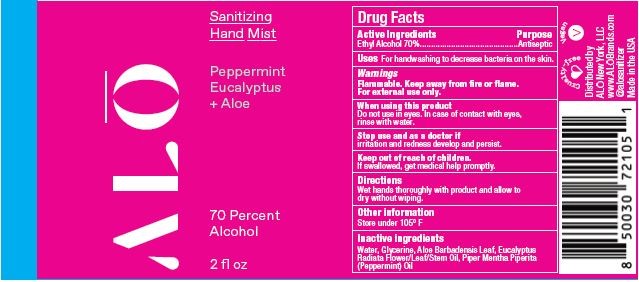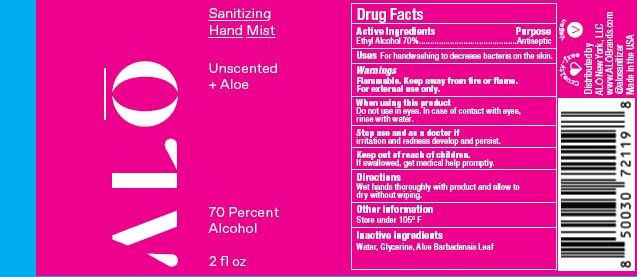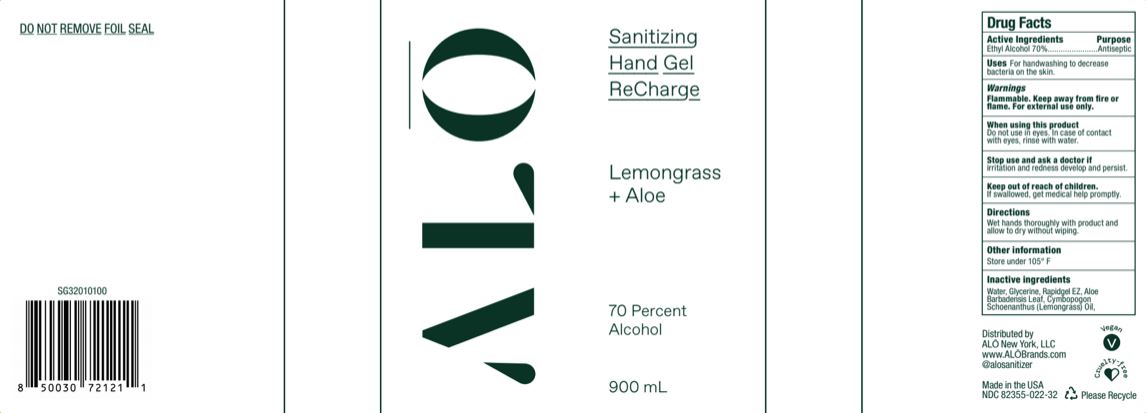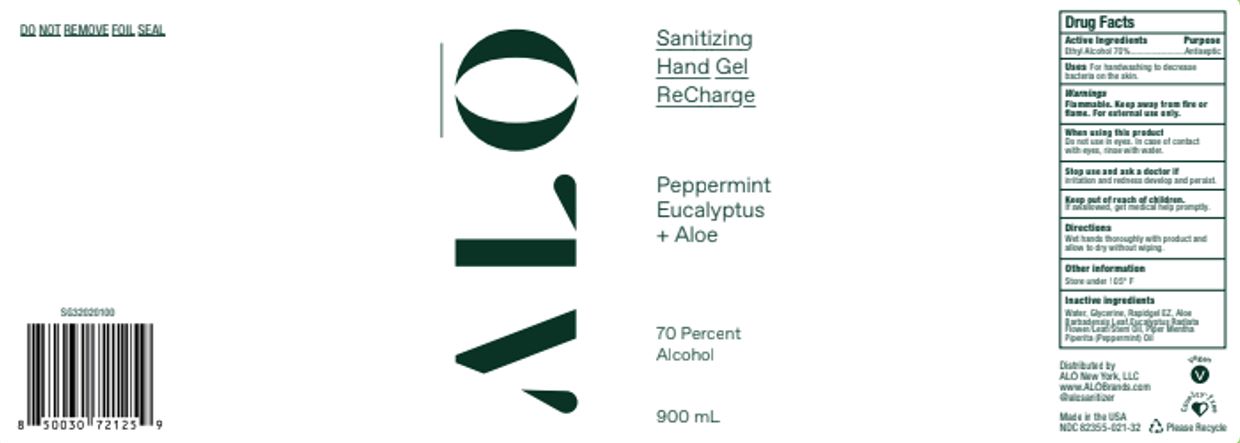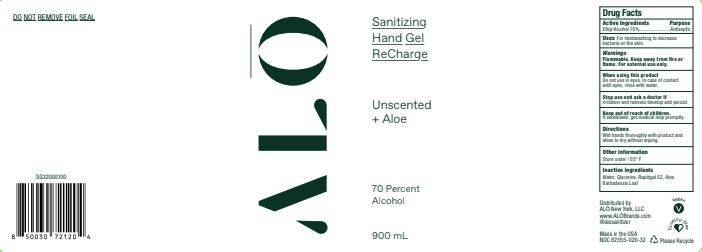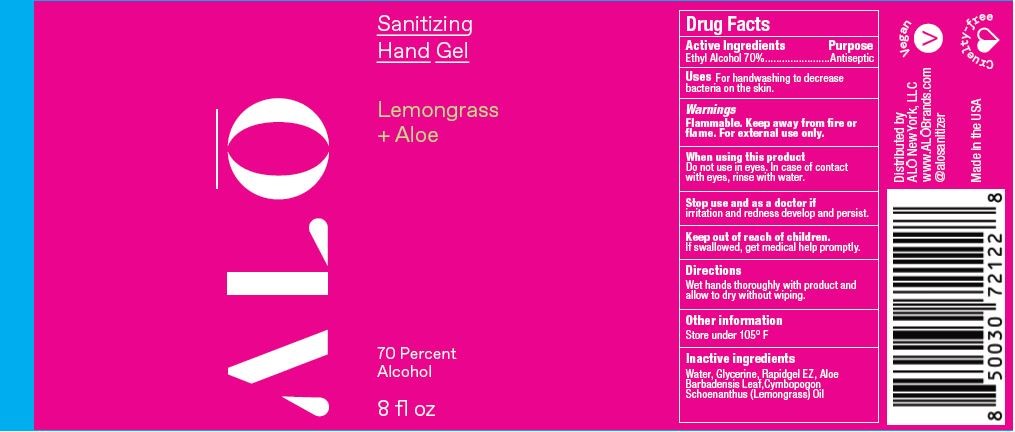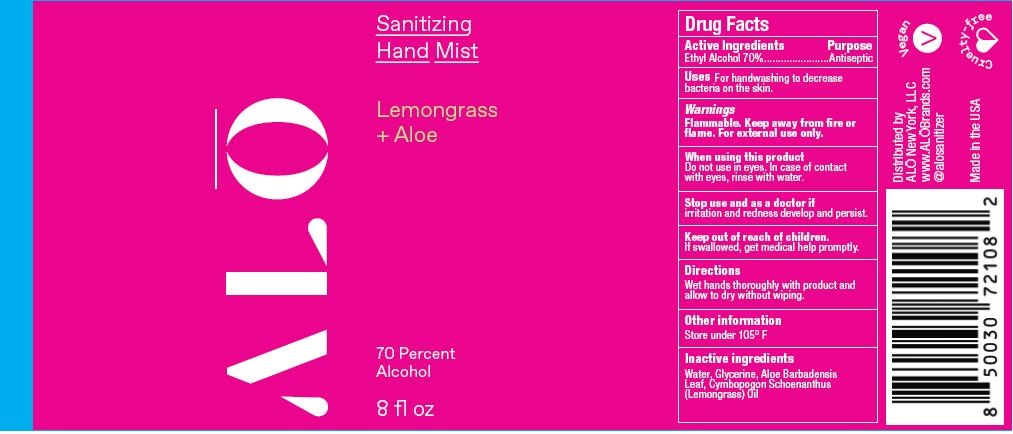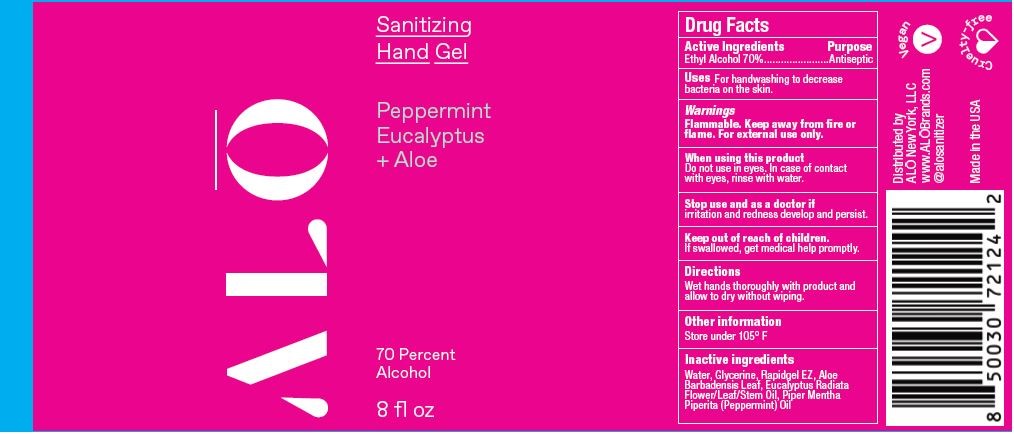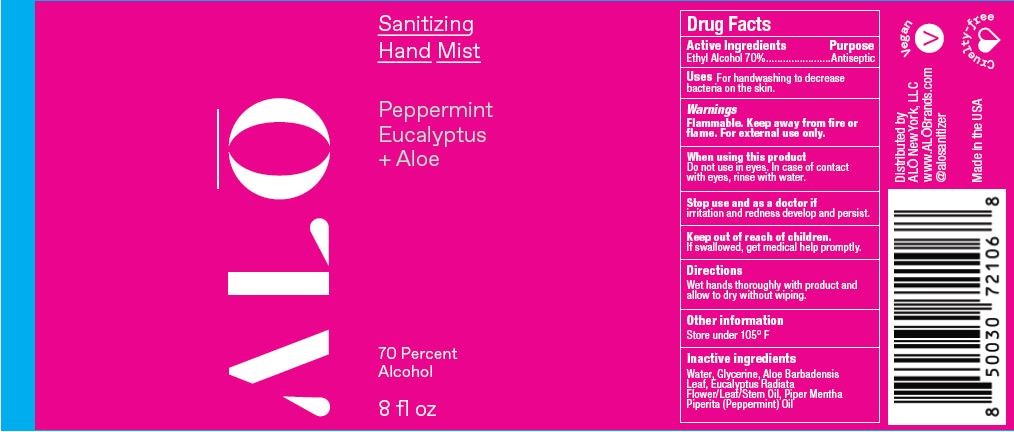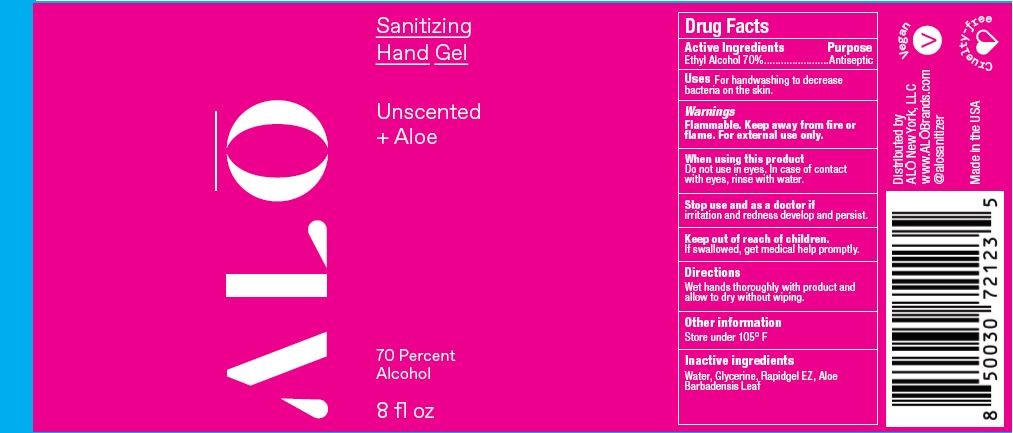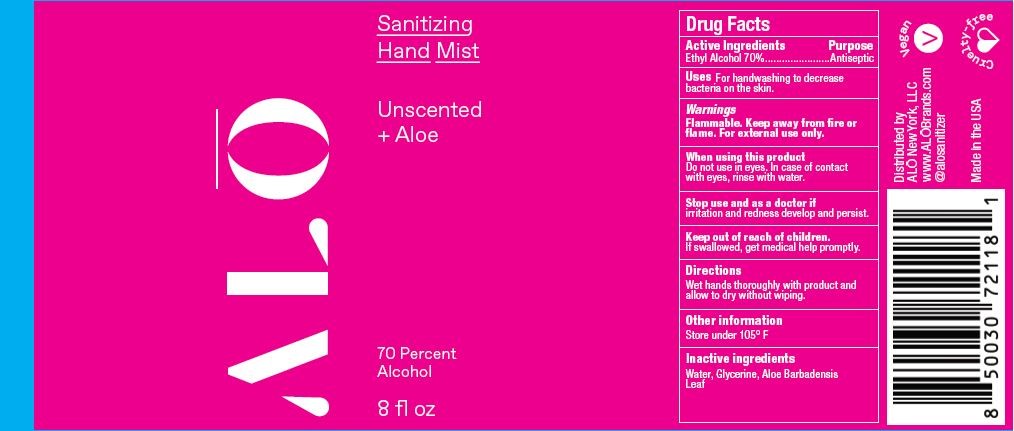 DRUG LABEL: Sanitizing Hand Mist - Unscented
NDC: 80588-010 | Form: SPRAY
Manufacturer: Alkaline Corporation
Category: otc | Type: HUMAN OTC DRUG LABEL
Date: 20240108

ACTIVE INGREDIENTS: ALCOHOL 70 mL/100 mL
INACTIVE INGREDIENTS: WATER; ALOE; GLYCERIN

ALOH Brands Hand Sanitizer

Active Ingredients

Ethyl Alcohol 70%

Purpose

Antiseptic

Uses

For handwashing to decrease bacteria on the skin

Warnings

Flammable. Keep away from fire or flame. For external use only.

When using this product

Do not use in eyes. In case of contact with eyes, rinse with water.

Stop use and ask a doctor if

irritation and redness develop and persist.

Keep out of reach of children.

If swallowed, get medical help promptly.

Directions

Wet hands thoroughly with product and allow to dry without wiping.

Other information

Store under 105°F

Inactive Ingredients

NDC 80588-010:

Water, Glycerine, Aloe Barbadensis Leaf

NDC 80588-011:

Water, Glycerine, Aloe Barbadensis Leaf, Eucalyptus Radiata Flower/Leaf/Stem Oil, Piper Mentha Piperita (Peppermint) Oil

NDC 80588-012:

Water, Glycerine, Aloe Barbadensis Leaf, Cymbopogon Schoenanthus (Lemongrass) Oil

NDC 80588-020:

Water, Glycerine, Rapidgel EZ, Aloe Barbadensis Leaf

NDC 80588-011:

Water, Glycerine, Rapidgel EZ, Aloe Barbadensis Leaf, Eucalyptus Radiata Flower/Leaf/Stem Oil, Piper Mentha Piperita (Peppermint) Oil

NDC 80588-012:

Water, Glycerine, Rapidgel EZ, Aloe Barbadensis Leaf, Cymbopogon Schoenanthus (Lemongrass) Oil